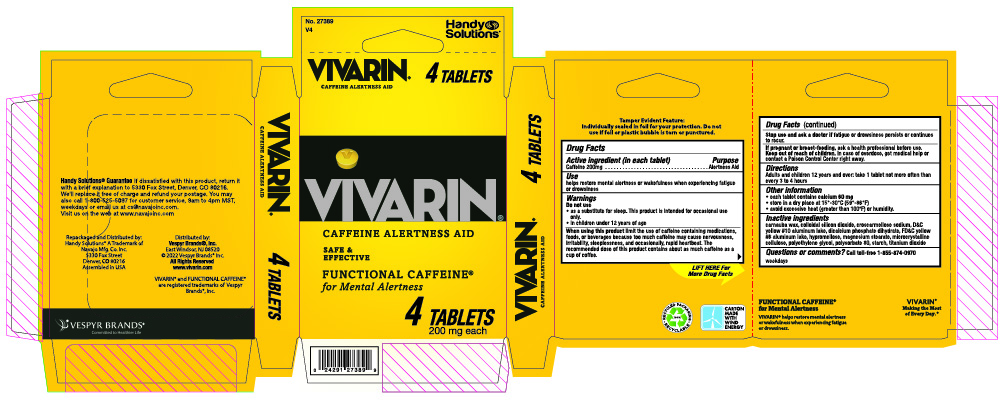 DRUG LABEL: Vivarin
NDC: 67751-226 | Form: TABLET
Manufacturer: Navajo Manufacturing Company Inc.
Category: otc | Type: HUMAN OTC DRUG LABEL
Date: 20241003

ACTIVE INGREDIENTS: CAFFEINE 200 mg/1 1
INACTIVE INGREDIENTS: CARNAUBA WAX; SILICON DIOXIDE; CROSCARMELLOSE SODIUM; D&C YELLOW NO. 10 ALUMINUM LAKE; DIBASIC CALCIUM PHOSPHATE DIHYDRATE; FD&C YELLOW NO. 6; HYPROMELLOSE, UNSPECIFIED; MAGNESIUM STEARATE; MICROCRYSTALLINE CELLULOSE; POLYETHYLENE GLYCOL, UNSPECIFIED; POLYSORBATE 80; STARCH, CORN; TITANIUM DIOXIDE

Vivarin

Drug Facts

Active ingredient (in each tablet)

Caffeine 200mg

Purpose

Alertness aid

Use

Helps restore mental alertness or wakefulness when experiencing fatigue or drowsiness

Warnings

Do not use

- as a substitute for sleep. This product is intended for occasional use only.
- in children under 12 years of age

When using this product

limit the use of caffeine-containing medications, foods, or beverages because too much caffeine may cause nervousness, irritability, sleeplessness, and occasionally, rapid heartbeat. The recommended dose of this product contains about as much caffeine as a cup of coffee.

Stop use and ask a doctor if

fatigue or drowsiness persists or continues to recur.

If pregnant or breast-feeding,

ask a health professional before use.

Keep out of reach of children.

In case of overdose, get medical help or contact a Poison Control Center right away.

Directions

Adults and children 12 years of age and over: take 1 tablet not more often than every 3 to 4 hours.

Other information

- each tablet contains calcium 60 mg
- store in a dry place at 15° - 30°C (59° - 86°F)
- avoid excessive heat (greater than 100°F) or humidity

Inactive ingredients

carnauba wax, colloidal silicon dioxide, croscarmellose sodium, D&C yellow #10 aluminum lake, dicalcium phosphate dihydrate, FD&C yellow #6 aluminum lake, hypromellose, magnesium stearate, microcrystalline cellulose, polyethylene glycol, polysorbate 80, starch, titanium dioxide

Questions or comments?

Call toll-free 1-855-874-0970 weekdays

PACKAGE LABEL-PRINCIPAL DISPLAY PANEL

Made in India